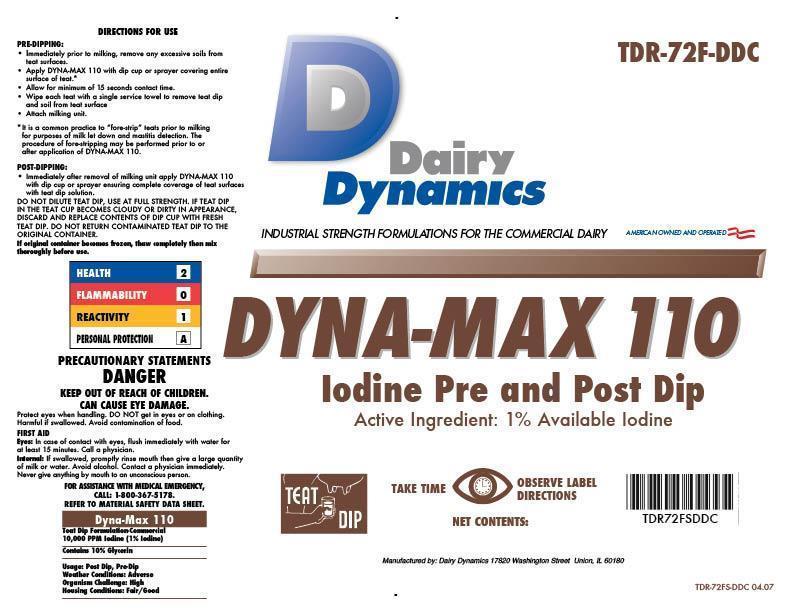 DRUG LABEL: DYNA-MAX 110
NDC: 67351-972 | Form: SOLUTION
Manufacturer: Dairy Dynamics L.L.C.
Category: animal | Type: OTC ANIMAL DRUG LABEL
Date: 20141118

ACTIVE INGREDIENTS: IODINE 10 g/1 L

DYNA-MAX 110

COMMERCIAL

Iodine Pre and Post Dip

Active Ingredient: 10,000 PPM Titratable Iodine

DIRECTIONS FOR USE

PRE-DIPPING

- Immediately prior to milking, remove any excessive soils from teat surfaces.
- Apply DYNA-MAX 110 with dip cup or sprayer covering the entire surface of the teat.*
- Allow for a minimum 15 seconds contact time.
- Wipe each teat with a single service towel to remove teat dip and soil from teat surface.
- Attach milking unit.

* It is common practice to “fore-strip” teats prior to milking for the purposes of milk letdown and mastitis detection. The procedure of fore-stripping may be performed prior to or after application of DYNA-MAX 110.

POST-DIPPING

Immediately after removal of milking unit apply DYNA-MAX 110 with a dip cup or sprayer ensuring complete coverage of teat surfaces with teat dip solution.

DO NOT DILUTE TEAT DIP, USE AT FULL STRENGTH. IF TEAT DIP IN THE TEAT CUP BECOMES CLOUDY OR DIRTY IN APPEARANCE, DISCARD AND REPLACE CONTENTS IF THE DIP CUP WITH FRESH TEAT DIP. DO NOT RETURN CONTAMINATED TEAT DIP TO THE ORIGINAL CONTAINER.

If original container becomes frozen, thaw completely then mix thoroughly before use.

PRECAUTIONARY STATEMENTS

DANGER

KEEP OUT OF REACH OF CHILDREN.

CAN CAUSE EYE DAMAGE.

Protect eyes when handling. DO NOT get in eyes or on clothing. Harmful is swallowed. Avoid contamination of food.

FIRST AID

Eyes: In case of contact with eyes, flush immediately with plenty of water for at least 15 minutes. Call a physician.

Internal: If swallowed, promptly rinse mouth with water then give a large quantity of milk or water. Avoid alcohol. Contact a physician immediately. Never give anything by mouth to an unconscious person.

FOR ASSISTANCE WITH MEDICAL EMERGENCY, CALL 1-800-367-5178.

REFER TO MATERIAL DATA SAFETY SHEET.

HEALTH - 2

FLAMMABILITY - 0

REACTIVITY - 1

PERSONAL PROTECTION - A

INDICATIONS AND USAGE

Dyna-Max 110

Teat Dip Formulation Commercial

10,000 PPM Iodine (1% Iodine)

Contains 10% Glycerin

Usage: Post Dip, Pre-Dip

Weather Conditions: Adverse

Organism Challenge: High

Housing Conditions: Fair/Good